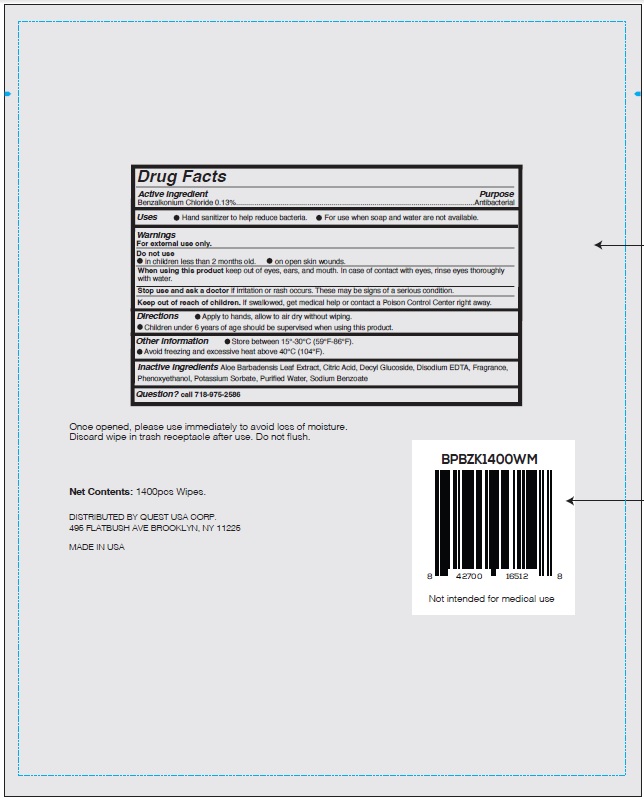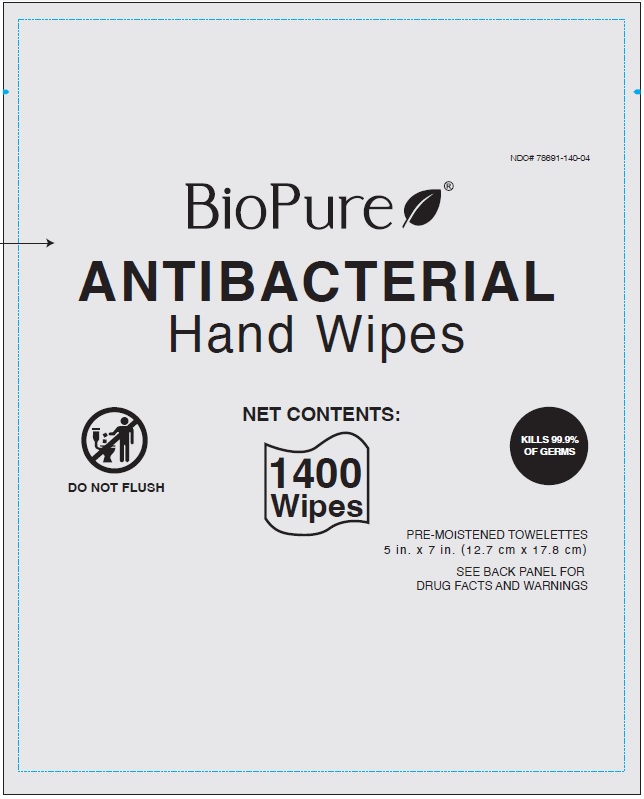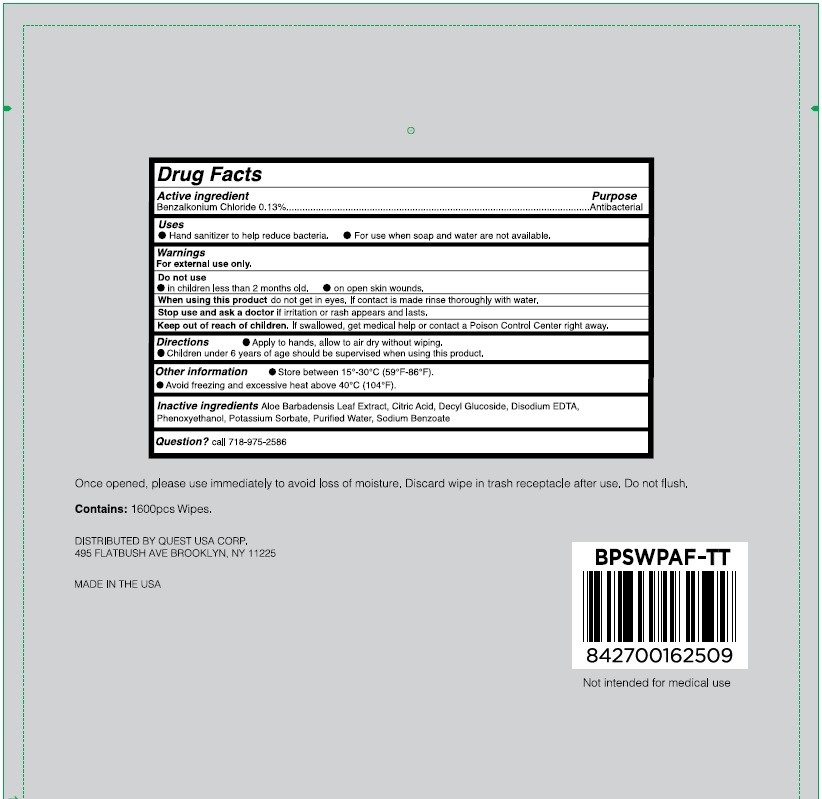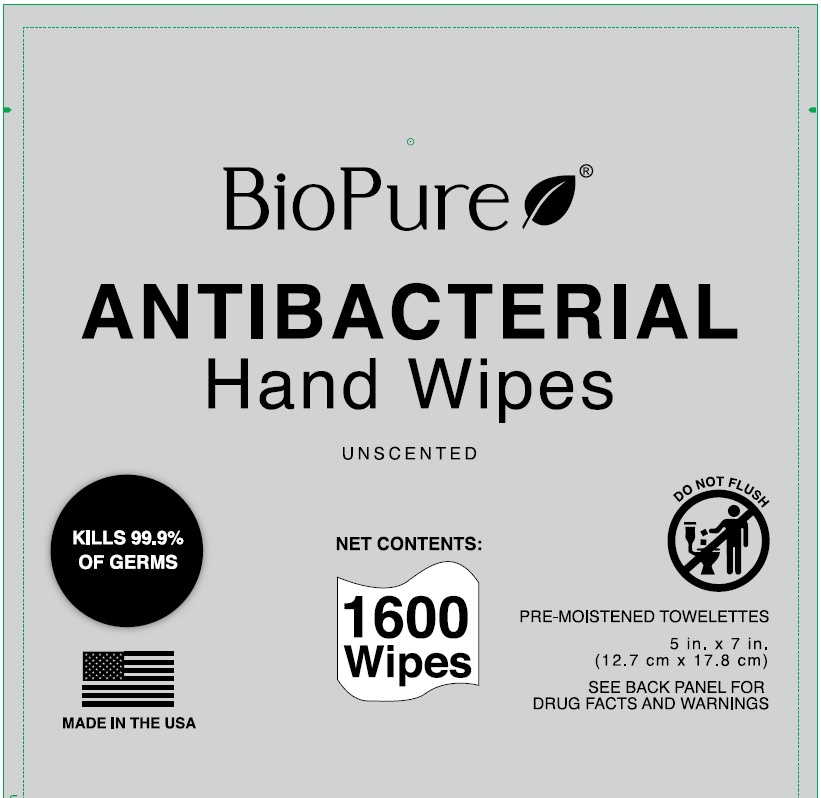 DRUG LABEL: Benzalkonium Chloride
NDC: 78691-140 | Form: CLOTH
Manufacturer: Quest USA Corp
Category: otc | Type: HUMAN OTC DRUG LABEL
Date: 20251205

ACTIVE INGREDIENTS: BENZALKONIUM CHLORIDE 0.13 g/100 1
INACTIVE INGREDIENTS: ALOE VERA LEAF; CITRIC ACID MONOHYDRATE; EDETATE DISODIUM ANHYDROUS; POTASSIUM SORBATE; PHENOXYETHANOL; WATER; SODIUM BENZOATE; DECYL GLUCOSIDE

Antibacterial Hand Wipes

Active ingredient

Benzalkonium Chloride 0.13%

Purpose

Antibacterial

Uses

- Hand sanitizer to help reduce bacteria
- For use when soap and water are not available

Warnings

For external use only.

Do not use

- in children less than 2 months old.
- on open skin wounds.

When using this product

keep out of eyes, ears, and mouth. In case of contact with eyes, rinse eyes thoroughly with water.

Stop use and ask a doctor

if irritation or rash occurs. These may be signs of serious condition.

Keep out of reach of children.

If swallowed, get medical help or contact a Poison Control Center right away.

Directions

- Apply to hands, allow to air dry without wiping.
- Children under 6 years of age should be supervised when using this product.

Other information

- Store in a cool, dry place, between 15°-30°C (59°F-86°F).
- Avoid freezing and excessive heat above 40°C (104°F).

Inactive ingredients

Aloe Barbadensis Leaf Extract, Citric Acid, Decyl Glucoside, Disodium EDTA, Fragrance, Phenoxyethanol, Potassium Sorbate, Purified Water, Sodium Benzoate

Questions?

call 718-975-2586

Principal Display Panel

BioPure

ANTIBACTERIAL

Hand Wipes

NET CONTENTS:

1400

Wipes

1600

Wipes